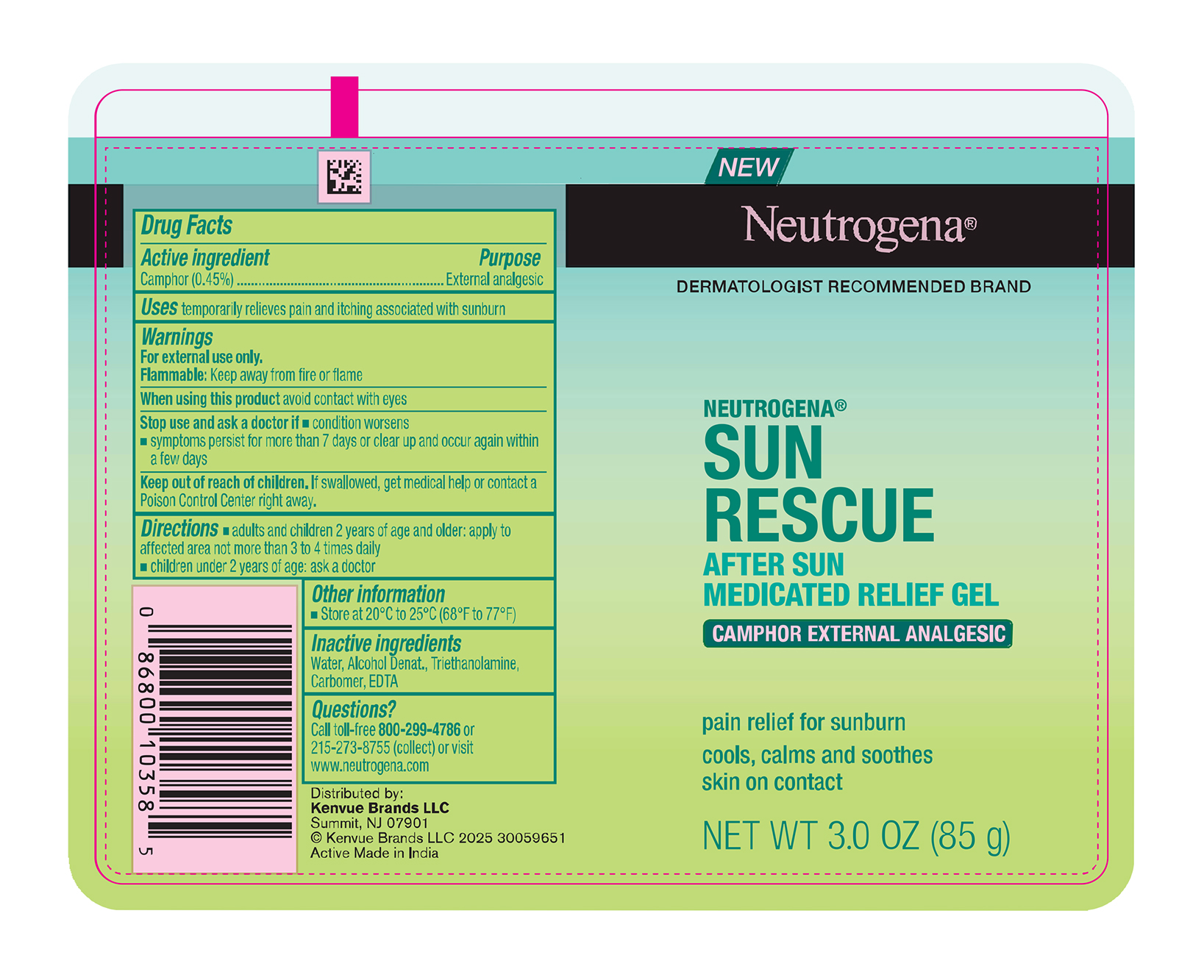 DRUG LABEL: Neutrogena Sun Rescue After Sun Medicated Relief
NDC: 69968-0721 | Form: GEL
Manufacturer: Kenvue Brands LLC
Category: otc | Type: HUMAN OTC DRUG LABEL
Date: 20250707

ACTIVE INGREDIENTS: CAMPHOR (SYNTHETIC) 4.5 mg/1 g
INACTIVE INGREDIENTS: CARBOXYPOLYMETHYLENE; EDETIC ACID; TROLAMINE; WATER; ALCOHOL

Neutrogena Sun Rescue After Sun Medicated Relief Gel

Drug Facts

Active ingredient

Camphor 0.45%

Purpose

External analgesic

Use

temporarily relieves pain and itching associated with sunburn

Warnings

For external use only.

Flammable: Keep away from fire or flame

When using this product avoid contact with eyes

Stop use and ask a doctor if

- condition worsens
- symptoms persist for more than 7 days or clear up and occur again within a few days

Keep out of reach of children. If swallowed, get medical help or contact a Poison Control Center right away.

Directions

- adults and children 2 years of age and older: apply to affected area not more than 3 to 4 times daily
- children under 2 years of age: ask a doctor

Other information

- Store at 20°C to 25°C (68°F to 77°F)

Inactive ingredients

Water, Alcohol Denat., Triethanolamine, Carbomer, EDTA

Questions?

Call toll-free 800-299-4786 or 215-273-8755 (collect) or visit www.neutrogena.com

Distributed by:

Kenvue Brands LLC
Summit, NJ 07901

PRINCIPAL DISPLAY PANEL - 85 g Tube Label

NEW

Neutrogena®

DERMATOLOGIST RECOMMENDED BRAND

NEUTROGENA®

SUN

RESCUE

AFTER SUN

MEDICATED RELIEF GEL

CAMPHOR EXTERNAL ANALGESIC

pain relief for sunburn

cools, calms and soothes

skin on contact

NET WT 3.0 OZ (85 g)